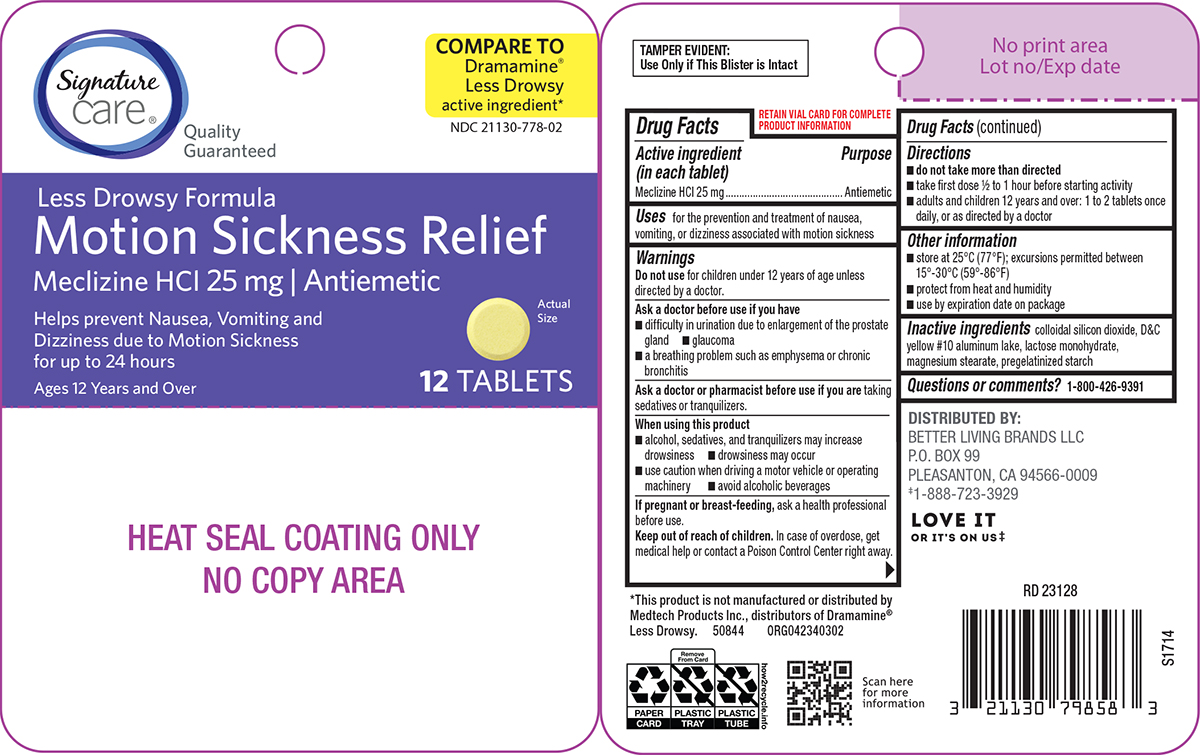 DRUG LABEL: Motion Sickness Relief
NDC: 21130-778 | Form: TABLET
Manufacturer: Better Living Brands, LLC
Category: otc | Type: HUMAN OTC DRUG LABEL
Date: 20251024

ACTIVE INGREDIENTS: MECLIZINE HYDROCHLORIDE 25 mg/1 1
INACTIVE INGREDIENTS: SILICON DIOXIDE; D&C YELLOW NO. 10 ALUMINUM LAKE; LACTOSE MONOHYDRATE; MAGNESIUM STEARATE; STARCH, CORN

Signature Care 44-403A

Active ingredient (in each tablet)

Meclizine HCl 25 mg

Purpose

Antiemetic

Uses

for the prevention and treatment of nausea, vomiting, or dizziness associated with motion sickness

Warnings

Do not use

for children under 12 years of age unless directed by a doctor.

Ask a doctor before use if you have

- glaucoma
- difficulty in urination due to enlargement of the prostate gland
- a breathing problem such as emphysema or chronic bronchitis

Ask a doctor or pharmacist before use if you are

taking sedatives or tranquilizers.

When using this product

- drowsiness may occur
- avoid alcoholic beverages
- alcohol, sedatives, and tranquilizers may increase drowsiness
- use caution when driving a motor vehicle or operating machinery

If pregnant or breast-feeding,

ask a health professional before use.

Keep out of reach of children.

In case of overdose, get medical help or contact a Poison Control Center right away.

Directions

- do not take more than directed
- take first dose 1/2 to 1 hour before starting activity
- adults and children 12 years and over: 1 to 2 tablets once daily, or as directed by a doctor

Other information

- store at 25°C (77°F); excursions permitted between 15°-30°C (59°-86°F)
- protect from heat and humidity
- use by expiration date on package

Inactive ingredients

colloidal silicon dioxide, D&C yellow #10 aluminum lake, lactose monohydrate, magnesium stearate, pregelatinized starch

Questions or comments?

1-800-426-9391

Principal Display Panel

Signature
Care®

Quality
Guaranteed

COMPARE TO
Dramamine®
Less Drowsy
active ingredient*

NDC 21130-778-02

Less Drowsy Formula
Motion Sickness Relief
Meclizine HCl 25 mg | Antiemetic

Helps prevent Nausea, Vomiting and
Dizziness due to Motion Sickness
for up to 24 hours

Ages 12 Years and Over

12 TABLETS

Actual
Size

TAMPER EVIDENT: Use Only if This Blister is Intact

*This product is not manufactured or distributed by
Medtech Products Inc., distributors of Dramamine®
Less Drowsy. 50844 ORG042340302

DISTRIBUTED BY:
BETTER LIVING BRANDS LLC
P.O. BOX 99
PLEASANTON, CA 94566-0009
‡1-888-723-3929

Signature Care 44-403A